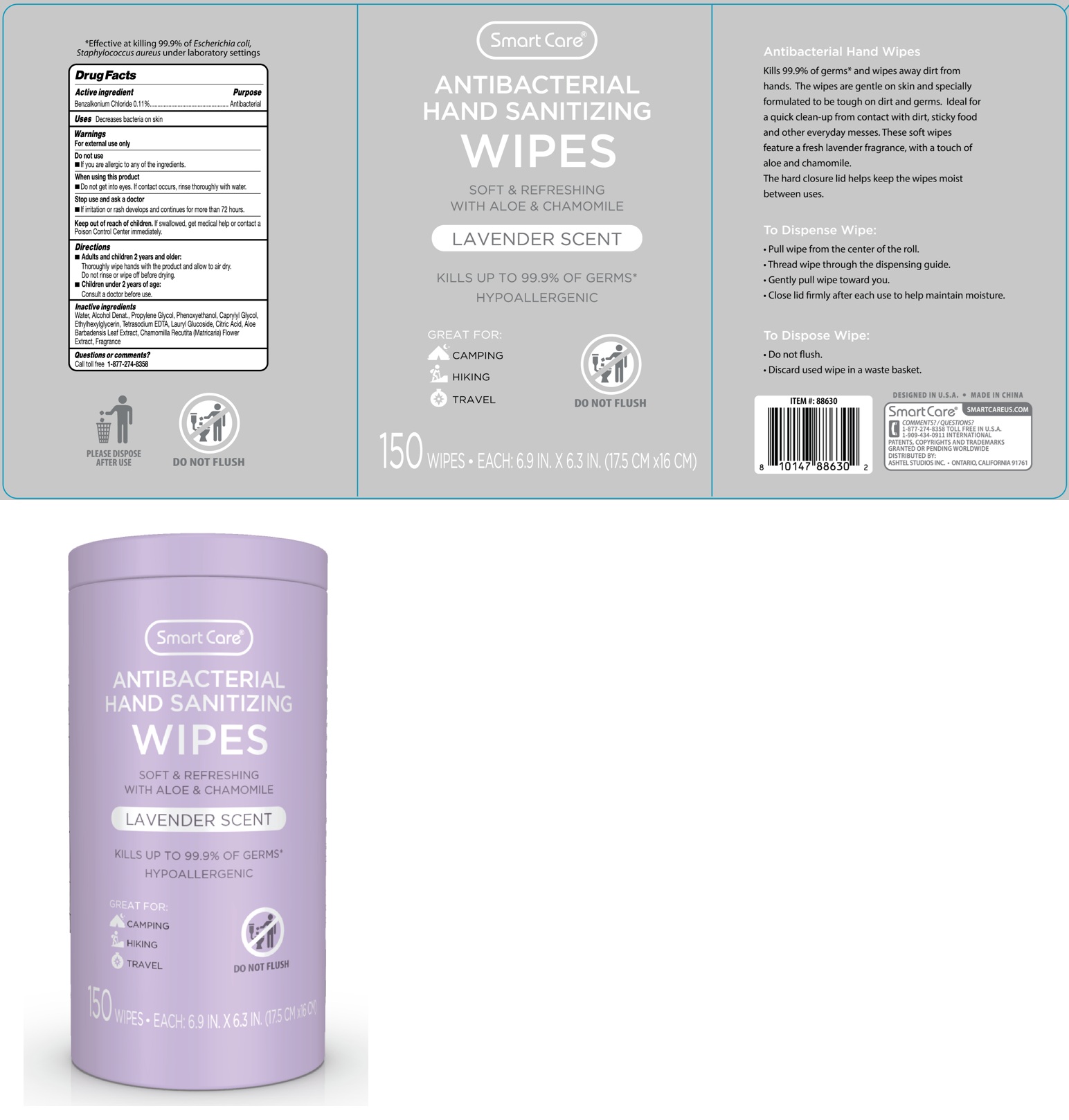 DRUG LABEL: Smart Care ANTIBACTERIAL HAND SANITIZING WIPES LAVENDER SCENT
NDC: 70108-208 | Form: CLOTH
Manufacturer: Ashtel Studios, Inc.
Category: otc | Type: HUMAN OTC DRUG LABEL
Date: 20250726

ACTIVE INGREDIENTS: BENZALKONIUM CHLORIDE 0.11 g/100 mL
INACTIVE INGREDIENTS: WATER; ALCOHOL; PROPYLENE GLYCOL; PHENOXYETHANOL; CAPRYLYL GLYCOL; ETHYLHEXYLGLYCERIN; EDETATE SODIUM; LAURYL GLUCOSIDE; CITRIC ACID MONOHYDRATE; ALOE VERA LEAF; CHAMOMILE

Smart Care® ANTIBACTERIAL HAND SANITIZING WIPES LAVENDER SCENT

Active ingredient

Benzalkonium Chloride 0.11%

Purpose

Antibacterial

Uses

Decreases bacteria on skin

Warnings

For external use only

Do not use
• If you are allergic to any of the ingredients.

When using this product
• Do not get into eyes. If contact occurs, rinse thoroughly with water.

Stop use and ask a doctor
• If irritation or rash develops and continues for more than 72 hours.

Keep out of reach of children. If swallowed, get medical help or contact a Poison Control Center immediately.

Directions

• Adults and children 2 years and older:
Thoroughly wipe hands with the product and allow to air dry.
Do not rinse or wipe off before drying.

• Children under 2 years of age:
Consult a doctor before use.

Inactive ingredients

Water, Alcohol Denat., Propylene Glycol, Phenoxyethanol, Caprylyl Glycol, Ethylhexylglycerin, Tetrasodium EDTA, Lauryl Glucoside, Citric Acid, Aloe Barbadensis Leaf Extract, Chamomilla Recutita (Matricaria) Flower Extract, Fragrance

Questions or comments?

Call toll free 1-877-274-8358

SOFT & REFRESHING WITH ALOE & CHAMOMILE

KILLS UP TO 99.9% OF GERMS*

HYPOALLERGENIC

GREAT FOR:
CAMPING
HIKING
TRAVEL

Antibacterial Hand Wipes
Kills 99.9% of germs* and wipes away dirt from hands. The wipes are gentle on skin and specially formulated to be tough on dirt and germs. Ideal for a quick clean-up from contact with dirt, sticky food and other everyday messes. These soft wipes feature a fresh lavender fragrance, with a touch of aloe and chamomile.
The hard closure lid helps keep the wipes moist between uses.

To Dispense Wipe:
• Pull wipe from the center of the roll.
• Thread wipe through the dispensing guide.
• Gently pull wipe toward you.
• Close lid firmly after each use to help maintain moisture.

To Dispose Wipe:
• Do not flush.
• Discard used wipe in a waste basket.

DESIGNED IN U.S.A. • MADE IN CHINA

Smart Care® SMARTCAREUS.COM

1-909-434-0911 INTERNATIONAL

PATENTS, COPYRIGHTS AND TRADEMARKS GRANTED OR PENDING WORLDWIDE

DISTRIBUTED BY:
ASHTEL STUDIOS INC. • ONTARIO, CALIFORNIA 91761

*Effective at killing 99.9% of Escherichia coli, Staphylococcus aureus under laboratory settings

PLEASE DISPOSE AFTER USE